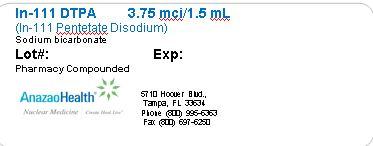 DRUG LABEL: In-111 DTPA
NDC: 51808-125 | Form: SOLUTION
Manufacturer: AnazaoHealth Corporation
Category: prescription | Type: HUMAN PRESCRIPTION DRUG LABEL
Date: 20120619

ACTIVE INGREDIENTS: INDIUM IN-111 PENTETATE DISODIUM 3.75 mCi/1.5 mL
INACTIVE INGREDIENTS: SODIUM BICARBONATE

In-111 DTPA (In-111 Pentetate Disodium)

DESCRIPTION

In-111 DTPA is supplied as a sterile, pyrogen-free, isotonic, aqueous solution that is buffered to pH 7 to 8. At calibration time, each milliliter contains 2.5 mCi of Pentetate Indium Disodium In-111 (no carrier-added) and sodium bicarbonate for pH adjustment.

CHARACTERISTICS

Indium 111 decays by electron capture with a physical half-life of 67.9 hour. The energies of the photons that are useful for detection and imaging studies are:

Radiation Mean % Disintegration Mean Energy (keV)

Gamma-2 90.2 171.3

Gamma-3 94.0 245.4

INDICATIONS AND USAGE

In-111 DTPA is indicated for use in radionuclide cisternography

CLINICAL PHARMACOLOGY

After intrathecal administration, the In-111 DTPA is absorbed from the subarachnoid space and the remainder flows superiorly to the basal cisterns within 2 to 4 hours and subsequently will be apparent in the Sylvian cisterns, the interhemispheric cisterns, and over the cerebral convexities. In normal individuals, the it will have ascended to the parasagittal region within 24 hours with simultaneous partial or complete clearance of activity from the basal cisterns and Sylvian regions. In contrast to air, In-111 DTPA does not normally enter the cerebral ventricles

CONTRAINDICATIONS

There are no known contraindications

DOSAGE AND ADMINISTRATION

Extreme care must be exercised to assure aseptic conditions in intrathecal injections. The maximum recommended intrathecal dose in the average patient (70kg) is 18.5 megabecquerels (500 microcuries). The patient dose should be measured by a suitable radioactivity calibration system immediately prior to administration. Parenteral drug preparations should be inspected visually for particulate matter and discoloration prior to administration whenever solution and container permit.

Storage and Handling

Store vial in its lead shield at a temperature of 5-30º C. Do not freeze

PACKAGE LABEL.PRINCIPAL DISPLAY PANEL

Figure 1